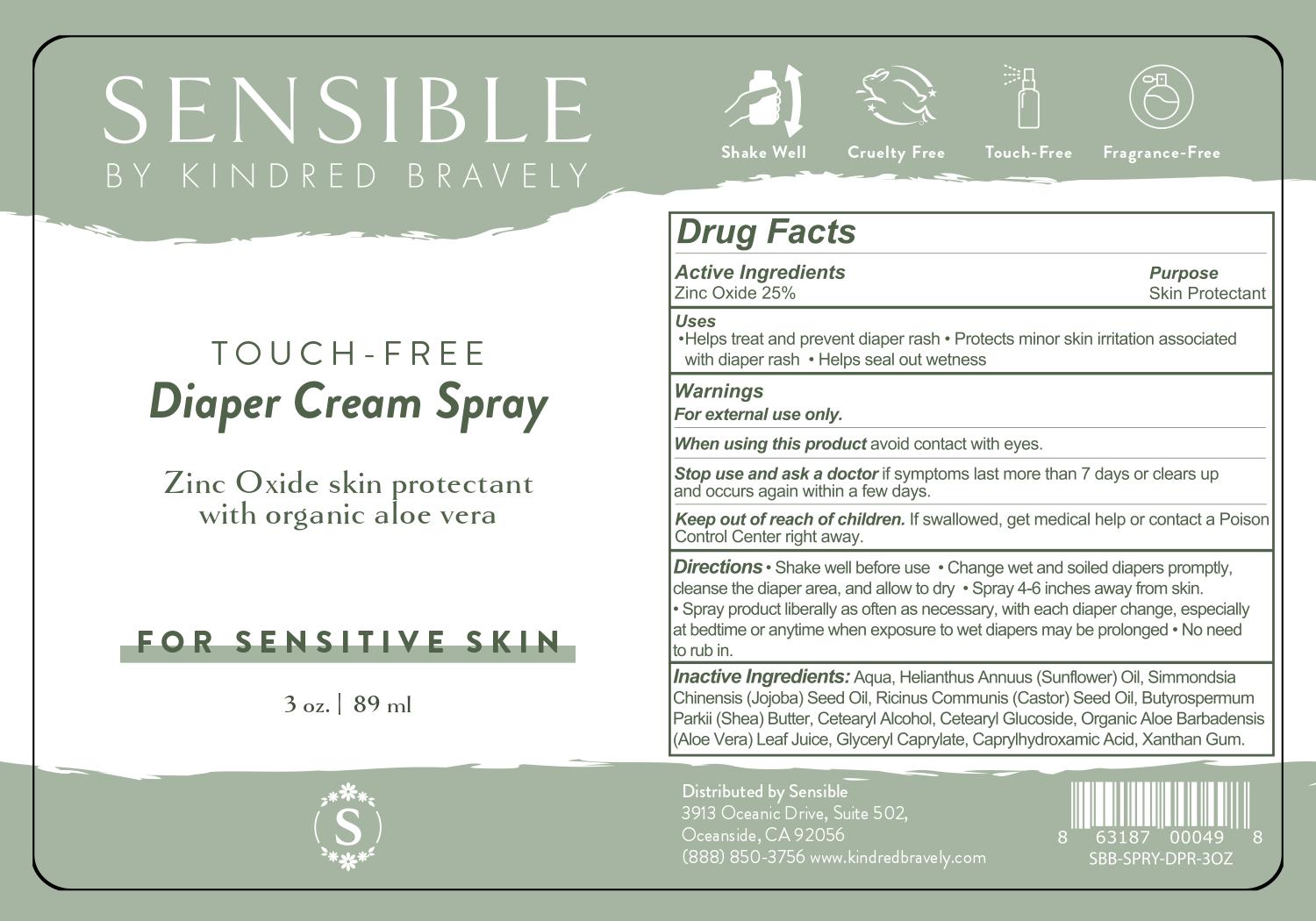 DRUG LABEL: Zinc Oxide
NDC: 82751-103 | Form: SPRAY, SUSPENSION
Manufacturer: Kindred Bravely
Category: otc | Type: HUMAN OTC DRUG LABEL
Date: 20220531

ACTIVE INGREDIENTS: ZINC OXIDE 250 mg/1 mL
INACTIVE INGREDIENTS: CASTOR OIL; SHEA BUTTER; CETEARYL GLUCOSIDE; GLYCERYL CAPRYLATE; WATER O-18; SUNFLOWER OIL; CAPRYLHYDROXAMIC ACID; XANTHAN GUM; JOJOBA OIL; CETOSTEARYL ALCOHOL; ALOE VERA LEAF

Active Ingredient

Zinc Oxicd 25%

Purpose

Skin Protectant

Uses

Helps treat and prevent diaper rash
Protects minor skin irritation associated with diaper rash
Helps seal out wetness

WARNINGS

Warnings

For external use only

When using this product

avoid contact with eyes

Stop use and ask a doctor

if symptoms last more than 7 days or clears up and occurs again within a few days.

Keep out of reach of children

If swallowed get medical help or contact a Poison Control Center right away.

Directions

Shake well before use
Change wet and soiled diapers promptly, cleanse the diaper area, and allow to dry
Spray 4-6 inches away from skin.
Spray product liberally as often as necessary, with each diaper change, especially at bedtime or anytime when exposure to wet diapers may be prolonged
No need to rub in.

Inactive Ingredients

Aqua (Water), Helianthus annuus (Sunflower) Oil, Simmondsia chinensis (Jojoba) Seed Oil, Ricinus communis (Castor) Seed Oil, Butyrospermum parkii (Shea) Butter, Cetearyl Alcohol, Cetearyl Glucoside, Organic Aloe barbadensis (Aloe vera) Leaf Juice, Glyceryl Caprylate, Caprylhydroxamic Acid, Xanthan Gum.

QUESTIONS

Distributed by Sensible

3913 Oceanic Drive, Suite 502

Oceanside, CA 92056

888-850-3756

www.kindredbravely.com